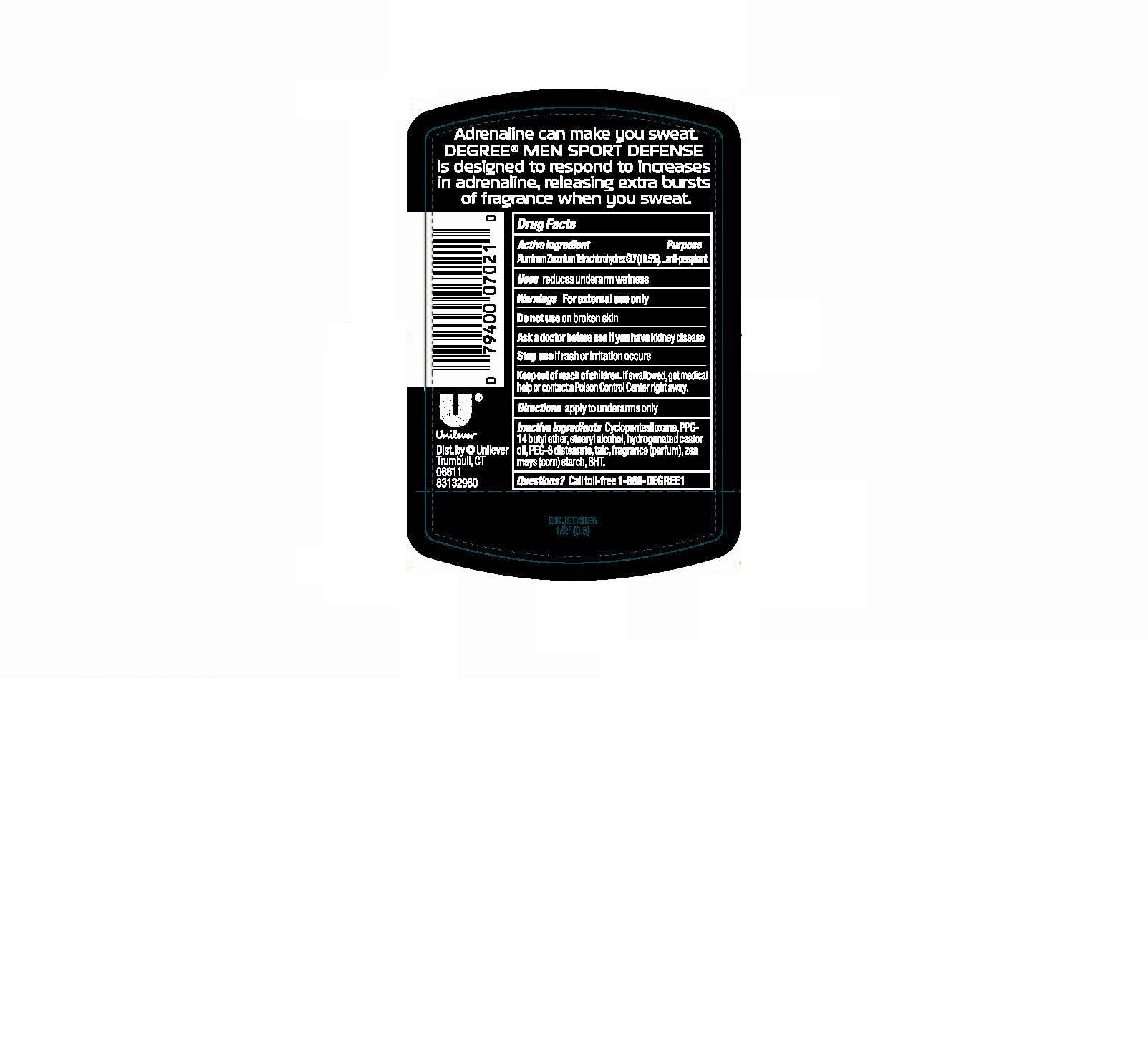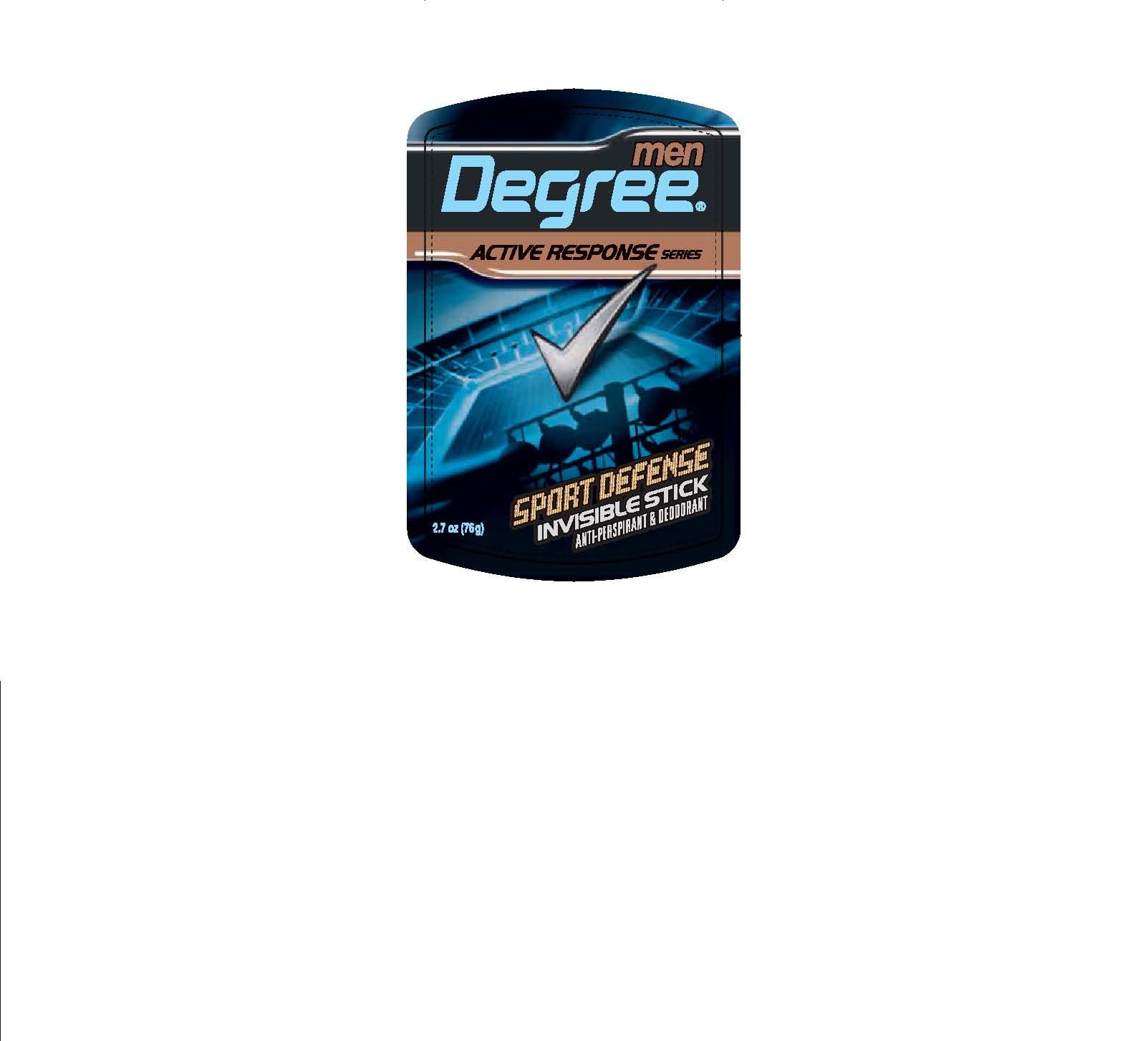 DRUG LABEL: Degree Men
NDC: 64942-1105 | Form: STICK
Manufacturer: Conopco Inc. d/b/a Unilever
Category: otc | Type: HUMAN OTC DRUG LABEL
Date: 20090917

ACTIVE INGREDIENTS: Aluminum Zirconium Tetrachlorohydrex GLY 18.5 g/100 g

Front and Back PDP for 2.7 oz Degree Men Sport Defense IS AP and Deod., and drug facts

Active Ingredient Purpose

Aluminum Zirconium Tetrachlorohydrex GLY (18.5%).................anti-perspirant

Warnings For External Use only

INACTIVE INGREDIENT

Cyclopentasiloxane, PPG-14 butyl ether, stearyl alcohol, hydrogenated castor oil, talc, PEG-8 distearate, fragrance (parfum), zea mays (corn) starch, BHT.

Questions? Call toll-free 1-866-DEGREE1

Do not use on broken skin

Ask a doctor before use if you have kidney disease

Stop use if rash or irritation occurs

Keep out of reach of children. If swallowed, get medical help or contact a Poison Control Center right away.

PACKAGE LABEL

PDP front 2.7 oz

PACKAGE LABEL

PDP 2.7 oz back